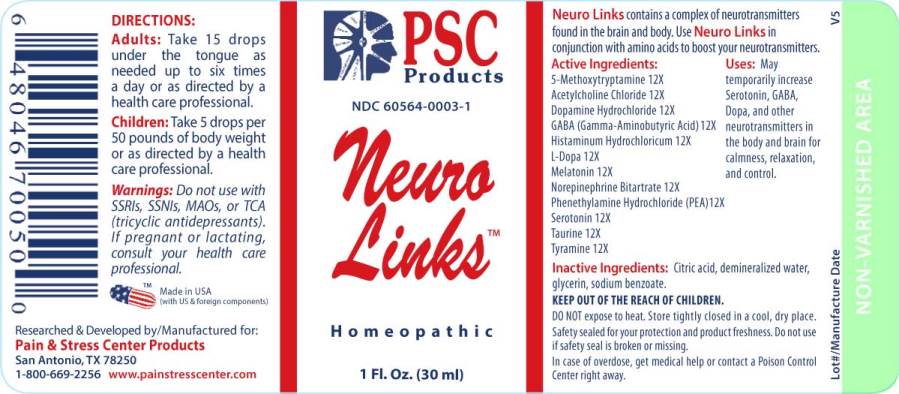 DRUG LABEL: Neuro Links
NDC: 60564-0003 | Form: LIQUID
Manufacturer: Pain & Stress Center Products
Category: homeopathic | Type: HUMAN OTC DRUG LABEL
Date: 20240110

ACTIVE INGREDIENTS: 5-METHOXYTRYPTAMINE 12 [hp_X]/1 mL; ACETYLCHOLINE CHLORIDE 12 [hp_X]/1 mL; DOPAMINE HYDROCHLORIDE 12 [hp_X]/1 mL; .GAMMA.-AMINOBUTYRIC ACID 12 [hp_X]/1 mL; HISTAMINE DIHYDROCHLORIDE 12 [hp_X]/1 mL; LEVODOPA 12 [hp_X]/1 mL; MELATONIN 12 [hp_X]/1 mL; NOREPINEPHRINE BITARTRATE 12 [hp_X]/1 mL; PHENETHYLAMINE HYDROCHLORIDE 12 [hp_X]/1 mL; SEROTONIN HYDROCHLORIDE 12 [hp_X]/1 mL; TAURINE 12 [hp_X]/1 mL; TYRAMINE 12 [hp_X]/1 mL
INACTIVE INGREDIENTS: CITRIC ACID MONOHYDRATE; WATER; GLYCERIN; SODIUM BENZOATE

DRUG FACTS:

ACTIVE INGREDIENTS:

5-Methoxytryptamine 12X, Acetylcholine Chloride 12X, Dopamine Hydrochloride 12X, GABA (Gamma-Aminobutyric Acid) 12X, Histaminum Hydrochloricum 12X, L-Dopa 12X, Melatonin 12X, Norepinephrine (Bitartrate) 12X, Phenethylamine (Hydrochloride) 12X, Serotonin (Hydrochloride) 12X, Taurine 12X, Tyramine 12X.

USES:

May temporarily increase Serotonin, GABA, Dopa, and other neurotransmitters in the body and brain for calmness, relaxation, and control.

WARNINGS:

Keep out of reach of children. In case of overdose, get medical help or contact Poison Control Center right away.

DO NOT expose to heat. Store tightly closed in a cool, dry place.

Safety sealed for your protection and product freshness. Do not use if safety seal is broken or missing.

In case of overdose, get medical help or contact Poison Control Center right away.

Do not use with SSRIs, SSNIs, MAOs, or TCA (tricyclic antidepressants). If pregnant or lactating, consult your health care professional.

Keep out of reach of children. In case of overdose, get medical help or contact Poison Control Center right away.

DIRECTIONS:

Adults: Take 15 drops under the tongue as needed up to six times a day or as directed by a health care professional.

Children: Take 5 drops per 50 pounds of body weight or as directed by a health care professional.

INDICATIONS:

May temporarily increase Serotonin, GABA, Dopa, and other neurotransmitters in the body and brain for calmness, relaxation, and control.

INACTIVE INGREDIENTS:

Citric Acid, Demineralized Water, Glycerin, Sodium Benzoate

QUESTIONS:

Researched & Developed by/Manufactured for:

Pain & Stress Center Products

San Antonio, TX 78250

1-800-669-2256 www.painstresscenter.com

PACKAGE LABEL DISPLAY:

PSC

Products

NDC 60564-0003-1

Neuro

Links

Homeopathic

1 Fl. Oz. (30 ml)